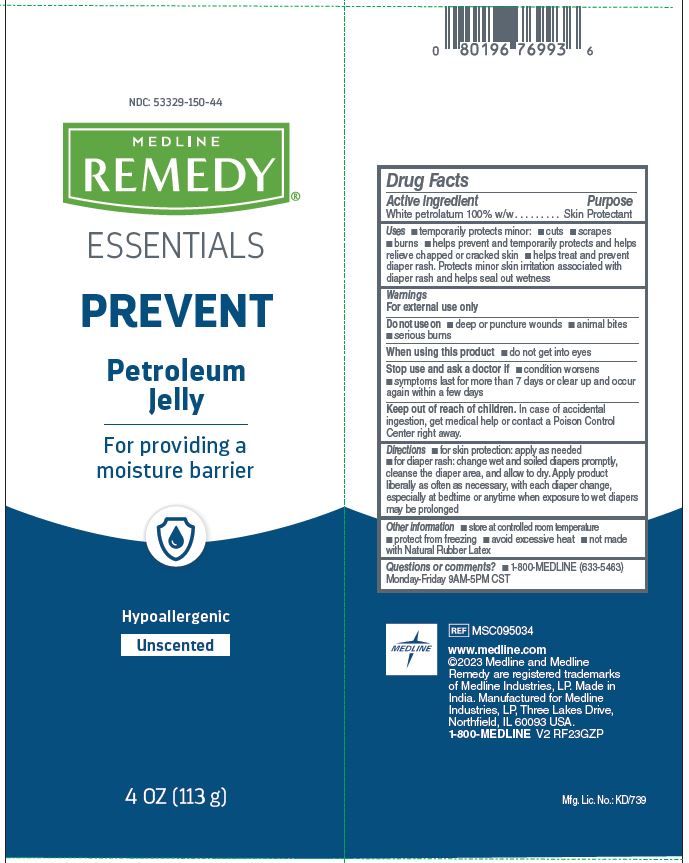 DRUG LABEL: Medline
NDC: 53329-150 | Form: JELLY
Manufacturer: Medline Industries, LP
Category: otc | Type: HUMAN OTC DRUG LABEL
Date: 20251120

ACTIVE INGREDIENTS: WHITE PETROLATUM 1 g/1 g
INACTIVE INGREDIENTS: WATER

150 Remedy Essentials Petroleum Jelly

Active ingredient

White petrolatum 100% w/w

Purpose

Skin protectant

Uses

- temporarily protects minor cuts, scrapes and burns
- helps prevent and temporarily protects and helps relieve chapped or cracked skin
- helps treat and prevent diaper rash. Protects minor skin irritation associated with diaper rash and helps seal out wetness

Warnings

For external use only

Do not use on

- deep or puncture wounds
- animal bites
- serious burns

When using this product

- do not get into eyes

Stop use and ask a doctor if

- condition worsens
- symptoms last for more than 7 days or clear up and occur again within a few days

Keep out of reach of children.

In case of accidental ingestion, get medical help or contact a Poison Control Center right away.

Directions

- for skin protection: apply as needed
- for diaper rash: change wet and soiled diapers promptly, cleanse the diaper area, and allow to dry. Apply product liberally as often as necessary , with each diaper change, especially at bedtime or anytime when exposure to wet diapers may be prolonged

Other information

- store at controlled room temperature
- protect from freezing
- avoid excessive heat
- not made with Natural Rubber Latex

Inactive ingredients

none

Questions or comments?

1-800-MEDLINE (633-5463)

Monday-Friday 9AM-5PM CST

Manufacturing Information

www.medline.com

©2023 Medline and Medline

Remedy are registered trademarks

of Medline Industries, LP.

Made in India

Manufactured for

Medline Industries, LP

Three Lakes Drive, Northfield, IL 60093 USA

1-800-MEDLINE

REF: MSC095034